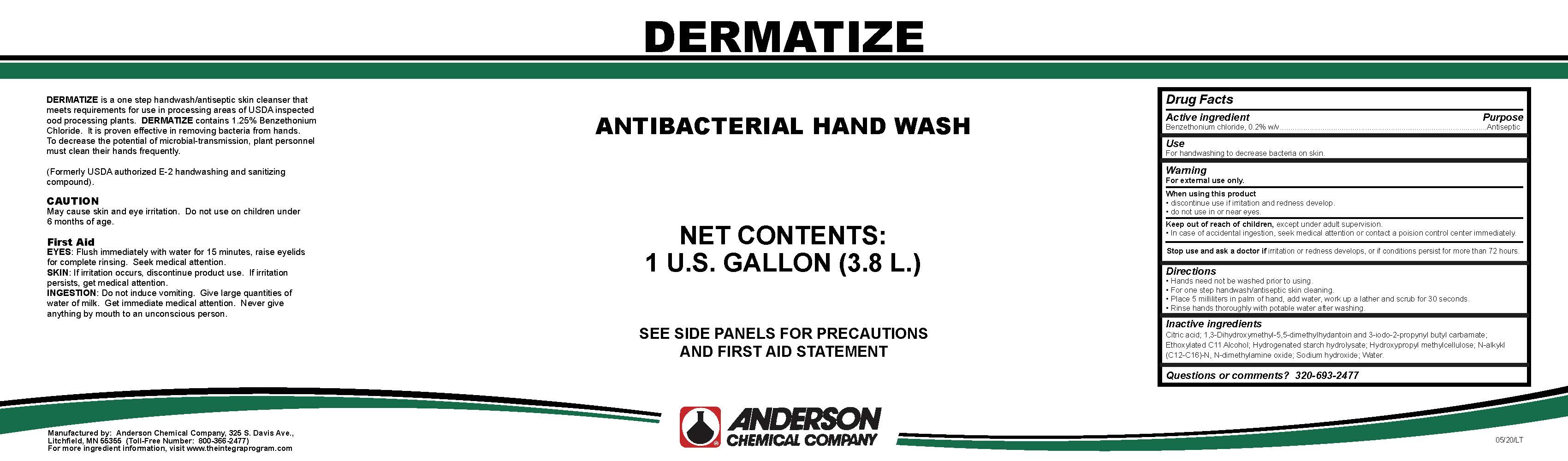 DRUG LABEL: Dermatize
NDC: 63131-0004 | Form: LIQUID
Manufacturer: Anderson Chemical Company
Category: otc | Type: HUMAN OTC DRUG LABEL
Date: 20200506

ACTIVE INGREDIENTS: BENZETHONIUM CHLORIDE 2 mg/1 mL
INACTIVE INGREDIENTS: HYDROXYMETHYL CELLULOSE; COCAMINE OXIDE; HYDROGENATED STARCH HYDROLYSATE; UNDECETH-7; WATER; ANHYDROUS CITRIC ACID; SODIUM HYDROXIDE; DMDM HYDANTOIN

Active ingredient

Benzethonium chloride, 0.2% w/v

Purpose

Antiseptic

Use

For handwashing to decrease bacteria on skin.

Warning

For external use only.

When using this product

- discontinue use if irritatio and redness develop.
- do not use in or near eyes.

Stop use and ask a doctor if irritation or redness develops, or if conditions persist for more than 72 hours.

Keep out of reach of children, except under adult supervision.

- In case of accidental ingestion, see medical attention or contact a poision control cernter immediately.

Directions

- Hands need not be washed prior to using.
- For one step hand wash/antiseptic skin cleaning.
- Place 5 milliliters in palm of hand, add water, work up a lather and scrub for 30 seconds.
- Rinse hands thoroughly with potable water after washing.

Inactive ingredients

Citric acid; 1,3-Dihydroxymethyl-5,5-dimethylhydantoin and 3-iodo-2-propynyl butyl carbamate; Ethoxylated C11 Alcohol; Hydrogenated starch hydrolysate; Hydroxypropyl methylcellulose; N-alkykl (C12-C16)-N, N-dimethylamine oxide; Sodium hydroxide; Water.

Questions or comments?

320-693-2477